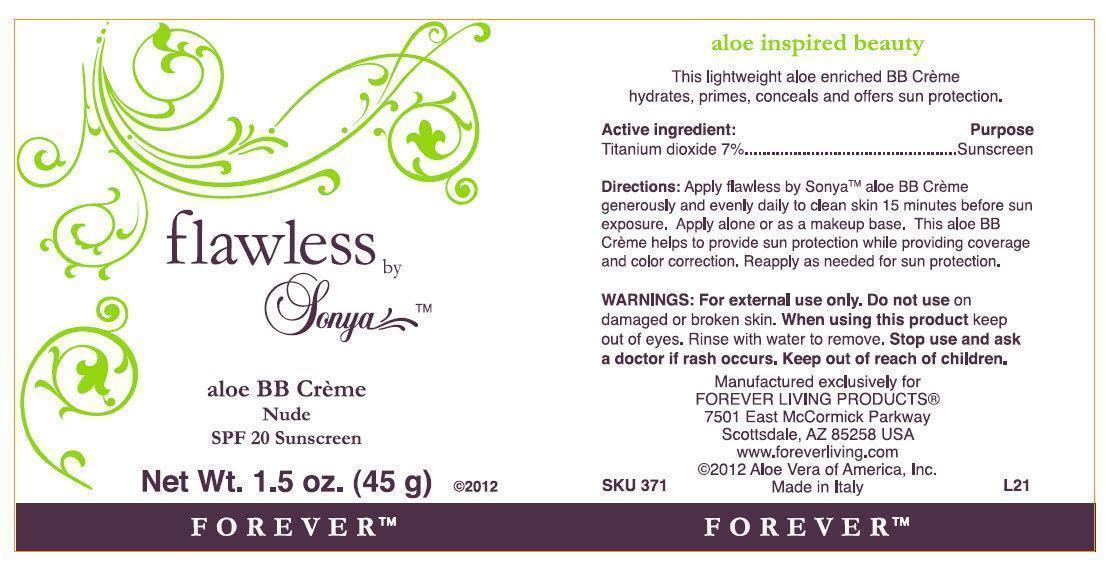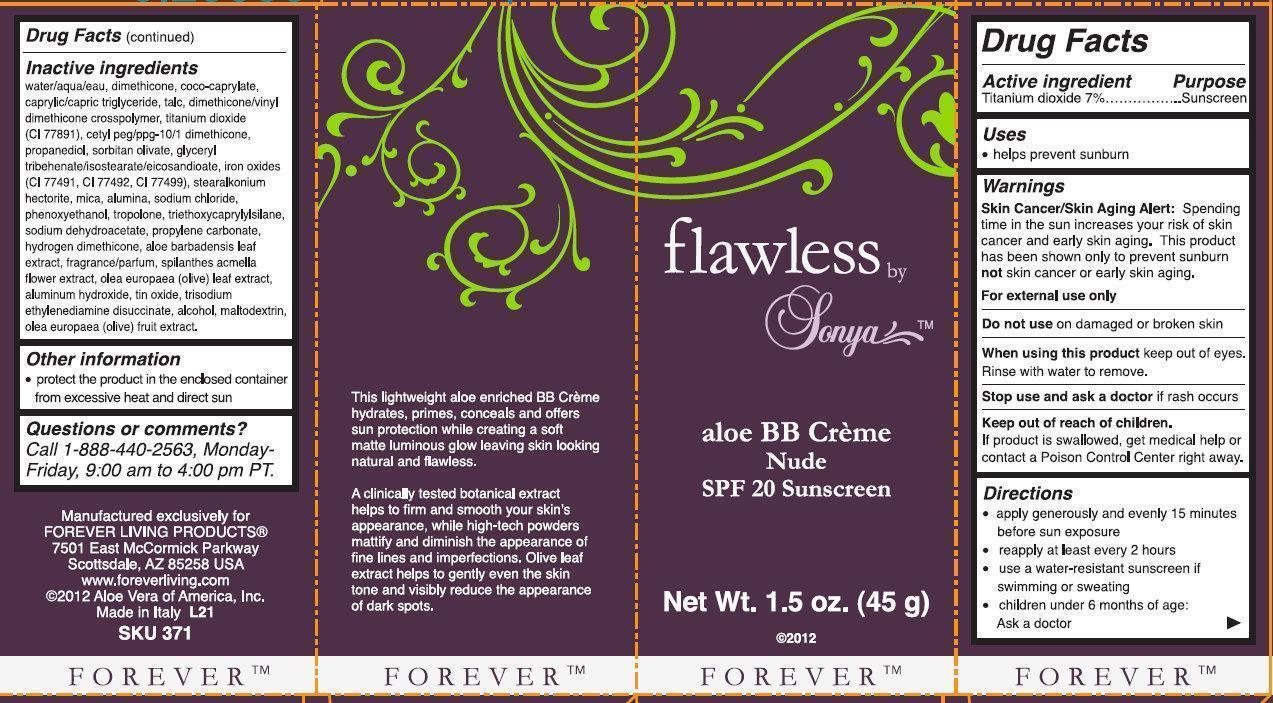 DRUG LABEL: flawless by Sonya aloe BB creme NUDE SPF 20 Sunscreen
                

NDC: 55891-001 | Form: CREAM
Manufacturer: Forever Living Products
Category: otc | Type: HUMAN OTC DRUG LABEL
Date: 20210422

ACTIVE INGREDIENTS: TITANIUM DIOXIDE 7 g/100 g
INACTIVE INGREDIENTS: WATER; DIMETHICONE; COCO-CAPRYLATE; MEDIUM-CHAIN TRIGLYCERIDES; TALC; DIMETHICONE/VINYL DIMETHICONE CROSSPOLYMER (SOFT PARTICLE); CETYL PEG/PPG-10/1 DIMETHICONE (HLB 5); PROPANEDIOL; SORBITAN OLIVATE; TRIBEHENIN; FERRIC OXIDE RED; FERRIC OXIDE YELLOW; FERROSOFERRIC OXIDE; MICA; ALUMINUM OXIDE; SODIUM CHLORIDE; PHENOXYETHANOL; TROPOLONE; TRIETHOXYCAPRYLYLSILANE; SODIUM DEHYDROACETATE; PROPYLENE CARBONATE; ALOE VERA LEAF; ACMELLA OLERACEA FLOWER; OLEA EUROPAEA LEAF; ALUMINUM HYDROXIDE; STANNIC OXIDE; TRISODIUM ETHYLENEDIAMINE DISUCCINATE; ALCOHOL; MALTODEXTRIN; BLACK OLIVE

flawless by Sonya aloe BB creme NUDE SPF 20 Sunscreen

Active ingredient

Titanium dioxide 7%

Purpose

Sunscreen

Uses

- helps prevent sunburn

Warnings

Skin Cancer/Skin Aging Alert: Spending time in the sun increases your risk of skin cancer and early skin aging. This product has been shown only to prevent sunburn not skin cancer or early skin aging.
For external use only

Do not use

on damaged or broken skin

When using this product

keep out of eyes. Rinse with water to remove.

Stop use and ask a doctor

if rash occurs

Keep out of reach of children.

If products is swallowed, get medical help or contact a Poison Control Center right away.

Directions

- apply generously and evenly 15 minutes before sun exposure
- reapply at least every 2 hours
- use a water-resistant sunscreen if swimming or sweating
- children under 6 months of age: Ask a doctor

Inactive ingredients

water/aqua/eau, dimethicone, coco-caprylate, caprylic/capric triglyceride, talc, dimethicone/vinyl dimethicone crosspolymer, titanium dioxide (CI 77891), cetyl peg/ppg-10/1 dimethicone, propanediol, sorbitan olivate, glyceryl tribehenate/isostearate/eicosandioate, iron oxides (CI 77491, CI 77492, CI 77499), stearalkonium hectorite, mica, alumina, sodium chloride, phenoxyethanol, tropolone, triethoxycaprylylsilane, sodium dehydroacetate, propylene carbonate, hydrogen dimethicone, aloe barbadensis leaf extract, fragrance/parfum, spilanthes acmella flower extract, olea europaea (olive) leaf extract, aluminum hydroxide, tin oxide, trisodium ethylenediamine disuccinate, alcohol, maltodextrin, olea europaea (olive) fruit extract.

Other information

- protect the product in the enclosed container from excessive heat and direct sun

Questions or comments?

Call 1-888-440-2563, Monday-Friday, 9:00 am to 4:00 pm PT.

FOREVER

This lightweight aloe enriched BB Creme hydrates, primes, conceals and offers sun protection while creating a soft matte luminous glow leaving skin looking natural and flawless.
A clinically tested botanical extract helps to firm and smooth your skin's appearance, while high-tech powders mattify and diminish the appearance of fine lines and imperfections. Olive leaf extract helps to gently even the skin tone and visibly reduce the appearance of dark spots.
Manufactured exclusively for
FOREVER LIVING PRODUCTS
7501 East McCormick Parkway
Scottsdale, AZ 85258 USA
www.foreverliving.com
2012 Aloe Vera of America, Inc.
Made in Italy L21
SKU 371

PACKAGE LABEL

flawless by Sonya aloe BB creme Nude SPF 20 Sunscreen Net Wt. 1.5 oz. (45g) 2012